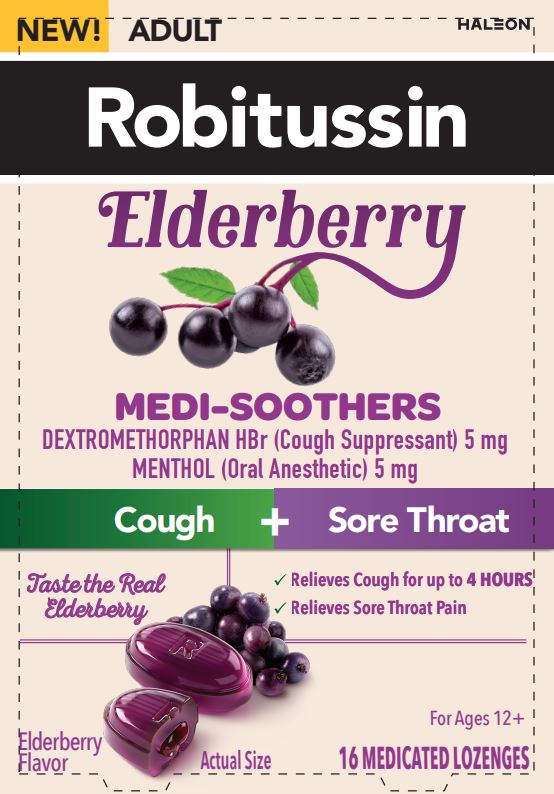 DRUG LABEL: Robitussin Medi-Soothers
NDC: 0031-9307 | Form: LOZENGE
Manufacturer: Haleon US Holdings LLC
Category: otc | Type: HUMAN OTC DRUG LABEL
Date: 20240406

ACTIVE INGREDIENTS: DEXTROMETHORPHAN HYDROBROMIDE 5 mg/1 1; MENTHOL, UNSPECIFIED FORM 5 mg/1 1
INACTIVE INGREDIENTS: CORN SYRUP; EUROPEAN ELDERBERRY JUICE; GLYCERIN; PROPYLENE GLYCOL; WATER; LECITHIN, SOYBEAN; SUCRALOSE; SUCROSE

Drug Facts

Active ingredients (in each lozenge)

Dextromethorphan HBr 5 mg

Menthol 5 mg

Purposes

Cough suppressant

Oral anesthetic

Uses

temporarily relieves

- cough due to minor throat and bronchial irritation as may occur with the common cold
- occasional minor irritation, pain, sore mouth, and sore throat

Warnings

Sore throat warning

- if sore throat is severe, persists for more than 2 days, is accompanied or followed by fever, headache, rash, swelling, nausea, or vomiting, consult a doctor promptly

Do Not Use

- if you are now taking prescription monoamine oxidase inhibitor (MAOI) (certain drugs for depression, psychiatric, or emotional conditions, or Parkinson’s disease), or for 2 weeks after stopping the MAOI drug. If you do not know if your prescription drug contains an MAOI, ask a doctor or pharmacist before taking this product.

Ask a doctor before use if you have

- persistent or chronic cough such as occurs with smoking, asthma, or emphysema
- cough that occurs with too much phlegm (mucus)

Stop use and ask a doctor or dentist if

- cough lasts more than 7 days, comes back, or is accompanied by fever, rash, or persistent headache. These could be signs of a serious condition.
- sore mouth symptoms do not improve in 7 days
- irritation, pain, or redness persists or worsens

Directions

- adults and children 12 years of age and older: take 2 lozenges (one immediately after the other) every 4 hours as needed. Allow each lozenge to dissolve slowly in the mouth.
- do not take more than 12 lozenges in any 24-hour period, or as directed by a doctor
- children under 12 years of age: do not use

Other information

- store at 20°-25°C (68°-77°F)

Inactive ingredients

corn syrup, elderberry juice concentrate, glycerin, natural flavors, propylene glycol, purified water, soy lecithin, sucralose, sucrose

Questions or comments?

call weekdays from 8 am to 6 pm EST at 1-800-245-1040

Additional Information

PARENTS:

Learn about teen medicine abuse

www.StopMedicineAbuse.org

Keep carton for complete information.

Do not use if blister is broken or damaged.

Distributed by: Haleon, Warren, NJ 07059

Trademarks owned or licensed by Haleon.

©2023 Haleon or licensor.

For more recent product information, visit www.robitussin.com

Principal Display Panel

NEW! ADULT

Robitussin

Elderberry

MEDI-SOOTHERS

DEXTROMETHORPHAN HBr (Cough Suppressant) 5 mg

Menthol (Oral Anesthetic) 5 mg

Cough + Sore Throat

Taste the Real Elderberry

- Relieves Cough for up to 4 HOURS
- Relieves Sore Throat Pain

Elderberry Flavor

Actual Size

For Ages 12+

16 MEDICATED LOZENGES

202559 Front Carton